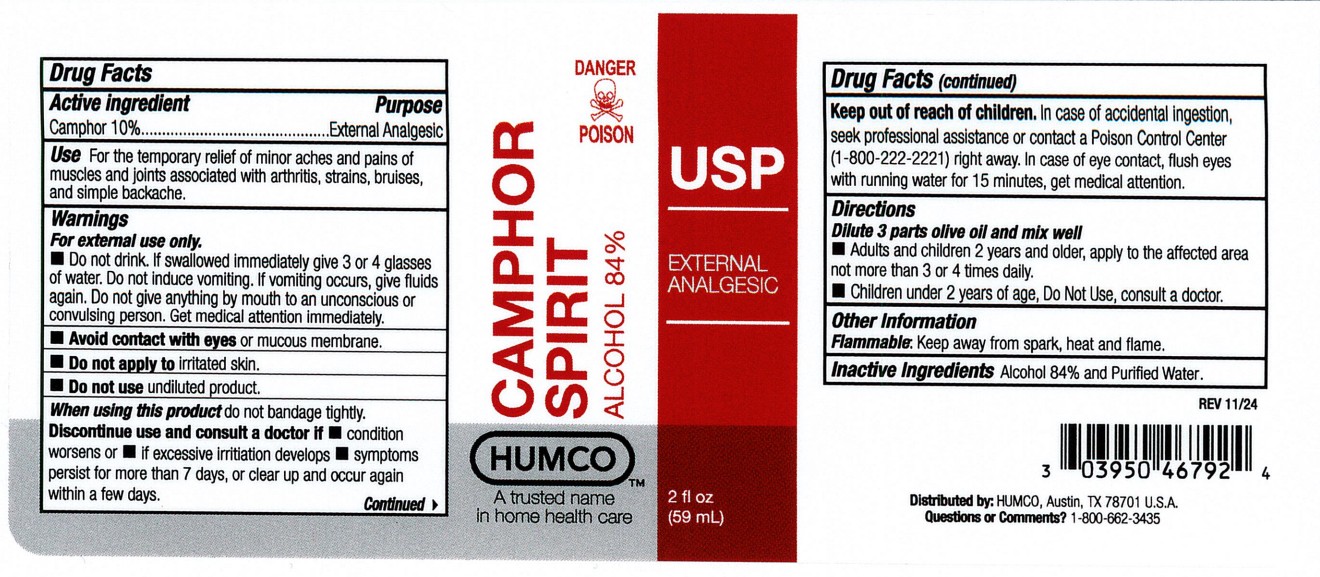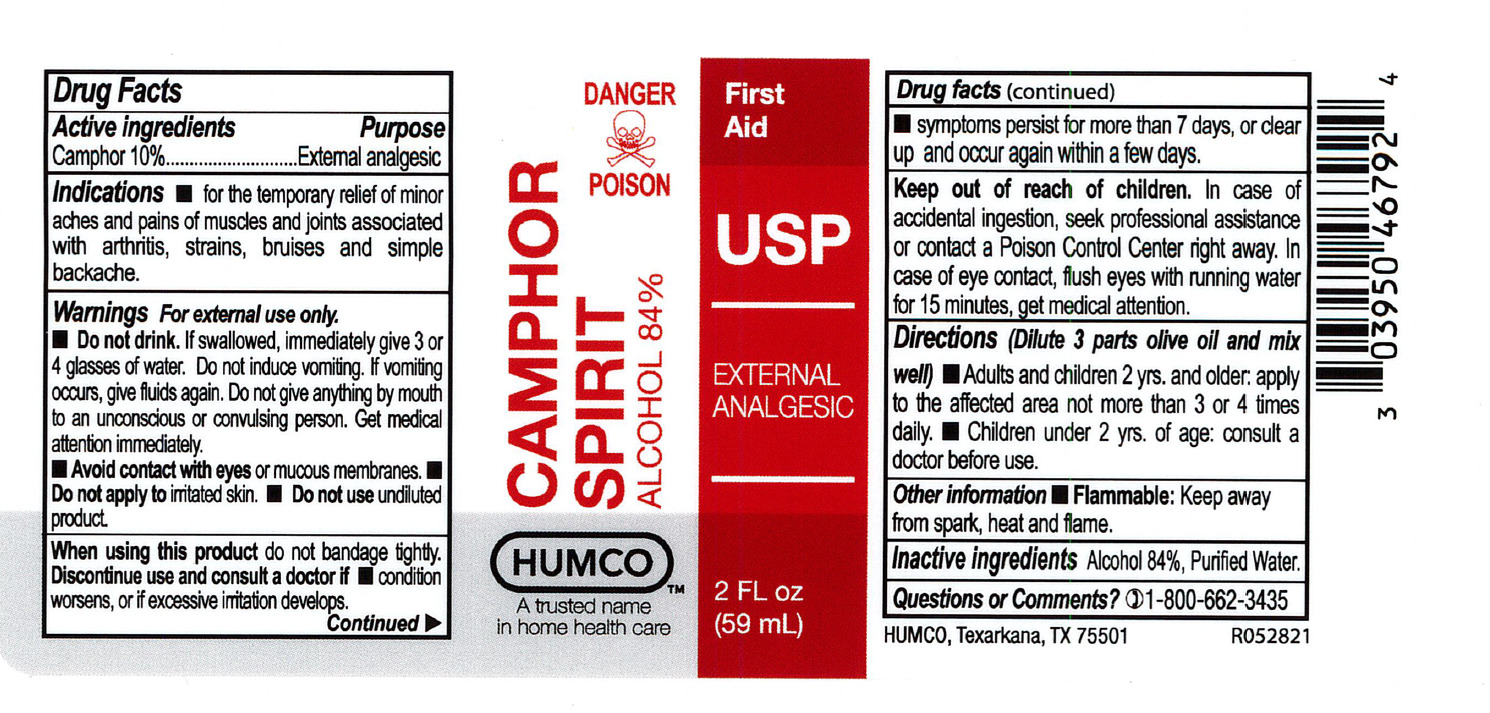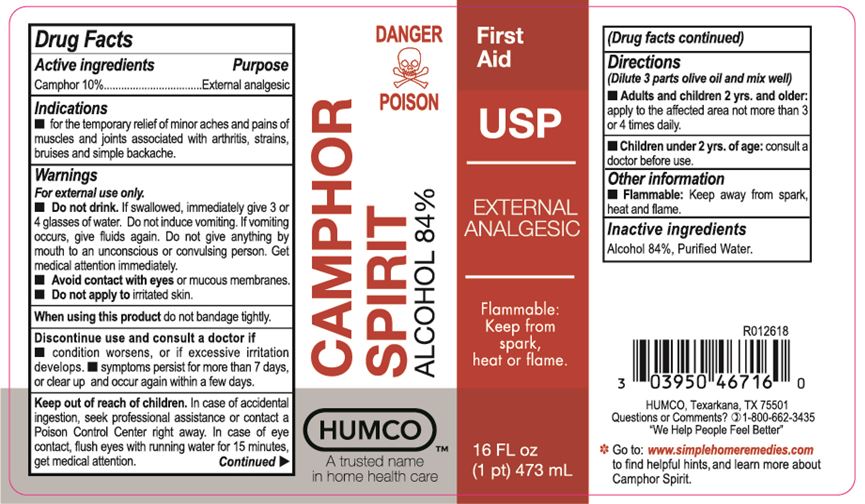 DRUG LABEL: HUMCO Camphor Spirit
NDC: 0395-0467 | Form: LIQUID
Manufacturer: Humco Holding Group, Inc.
Category: otc | Type: HUMAN OTC DRUG LABEL
Date: 20251211

ACTIVE INGREDIENTS: CAMPHOR (NATURAL) 100 mg/1 mL
INACTIVE INGREDIENTS: ALCOHOL; WATER

HUMCO Camphor Spirit

Drug Facts

Active Ingredient

Camphor 10%

Purpose

External analgesic

Use

For the temporary relief of minor aches, muscle and joint pain associated with arthritis, strains, brusies and simple backache.

Warnings

For external use only.

Do not drink. If swallowed, immediately give 3 or 4 glases of water. Do not induce vomiting. If vomiting occurs, give fluids again. Do not give anything by mouth to an unconscious or convulsing person. Get medical attention immediately.

Avoid contact with eyes or mucous membranes.

Do not apply to irritated skin.

Do not use undiluted product.

When using this product

Do not bandage tightly.

Discontinue use and consult a doctor if

condition worsens, or if excesive irritation develops.

symptoms persit for more than 7 days, or clear up and occur again within a few days.

Keep out of reach of children

In case of accidental ingestion, seek professional assistance or contact a Poison Control Center right away. In case of eye contact, flush eyes with running water for 15 minutes, get medical attention.

Directions

(dilute 3 parts olive oil and mix well)

Adults and children 2 yrs. and older. apply to th affected area not more than 3 or 4 times daily.

Children under 2 yrs of age: consult a doctor before use.

Other Information

Flammable: Keep away from spark, heat and flame.

Inactive ingredients

Alcohol 84%, Purified Water

Questions or Comments?

1-800-662-3435